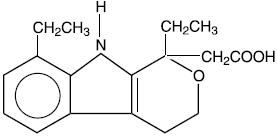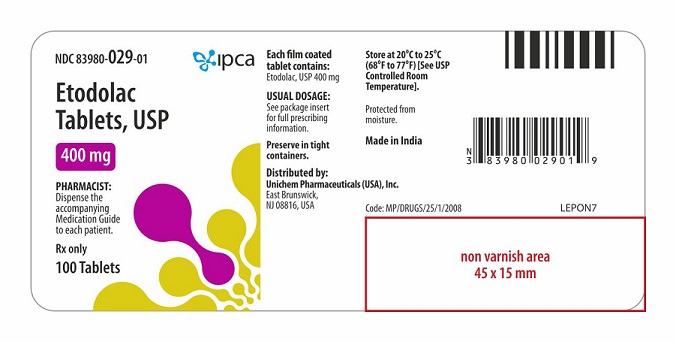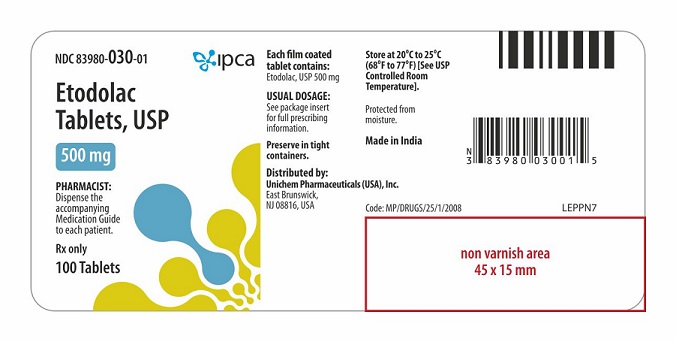 DRUG LABEL: etodolac
NDC: 83980-029 | Form: TABLET
Manufacturer: Ipca Laboratories Limited
Category: prescription | Type: HUMAN PRESCRIPTION DRUG LABEL
Date: 20260129

ACTIVE INGREDIENTS: ETODOLAC 400 mg/1 1
INACTIVE INGREDIENTS: CROSPOVIDONE; FERRIC OXIDE RED; FERRIC OXIDE YELLOW; HYPROMELLOSES; LACTOSE MONOHYDRATE; MAGNESIUM STEARATE; POLYETHYLENE GLYCOL 400; POVIDONE K30; SILICON DIOXIDE; SODIUM LAURYL SULFATE; TALC; TITANIUM DIOXIDE

Etodolac Tablets, USP

Rx only

BOXED WARNING

Cardiovascular Thrombotic Events

- Nonsteroidal anti-inflammatory drugs (NSAIDs) cause an increased risk of serious cardiovascular thrombotic events, including myocardial infarction and stroke, which can be fatal. This risk may occur early in treatment and may increase with duration of use [see Warnings and Precautions ].
- Etodolac tablets 400 mg and 500 mg are contraindicated in the setting of coronary artery bypass graft (CABG) surgery [see Contraindications and Warnings ].

Gastrointestinal Risk

- NSAIDs cause an increased risk of serious gastrointestinal adverse events including bleeding, ulceration, and perforation of the stomach or intestines, which can be fatal. These events can occur at any time during use and without warning symptoms. Elderly patients are at greater risk for serious gastrointestinal (GI) events. (See WARNINGS).

DESCRIPTION

Etodolac or etodolac tablets, USP is member of the pyranocarboxylic acid group of nonsteroidal anti-inflammatory drugs (NSAIDs). Each tablet contains etodolac for oral administration. Etodolac is a racemic mixture of [+]S and [-]R-enantiomers. Etodolac is a white or almost white crystalline powder, practically insoluble in water, freely soluble in acetone and ethanol [96%].

The chemical name is (±) 1,8-diethyl-1,3,4,9-tetrahydropyrano-[3,4-b]indole-1-acetic acid. The molecular weight of the base is 287.36. It has a pKa of 4.65 and an n-octanol: water partition coefficient of 11.4 at pH 7.4. The molecular formula for etodolac is C17H21NO3, and it has the following structural formula:

Each film coated tablet, for oral administration, contains 400 mg or 500 mg of etodolac, USP. In addition, each tablet contains the following inactive ingredients: colloidal silicon dioxide, crospovidone, hypromellose, iron oxide yellow, lactose monohydrate, magnesium stearate, polyethylene glycol, povidone, sodium lauryl sulphate, talc, and titanium dioxide. The 400 mg tablets also contain iron oxide red.

CLINICAL PHARMACOLOGY

Pharmacodynamics

Etodolac is a nonsteroidal anti-inflammatory drug (NSAID) that exhibits anti-inflammatory, analgesic, and antipyretic activities in animal models. The mechanism of action of etodolac, like that of other NSAIDs, is not completely understood, but may be related to the prostaglandin synthetase inhibition.

Etodolac is a racemic mixture of [-]R- and [+]S-etodolac. As with other NSAIDs, it has been demonstrated in animals that the [+]S-form is biologically active. Both enantiomers are stable and there is no [-]R to [+]S conversion in vivo.

Pharmacokinetics

Absorption

The systemic bioavailability of etodolac from etodolac tablets is 100% as compared to solution and at least 80% as determined from mass balance studies. Etodolac is well absorbed and had a relative bioavailability of 100% when 200 mg capsules were compared with a solution of etodolac. Based on mass balance studies, the systemic availability of etodolac from either the tablet or capsule formulation is at least 80%. Etodolac does not undergo significant first-pass metabolism following oral administration. Mean (± 1 SD) peak plasma concentrations (Cmax) range from approximately 14 ± 4 to 37 ± 9 mcg/mL after 200 to 600 mg single doses and are reached in 80 ± 30 minutes (see Table 1 for summary of pharmacokinetic parameters). The dose-proportionality based on the area under the plasma concentration-time curve (AUC) is linear following doses up to 600 mg every 12 hours. Peak concentrations are dose proportional for both total and free etodolac following doses up to 400 mg every 12 hours, but following a 600 mg dose, the peak is about 20% higher than predicted on the basis of lower doses. The extent of absorption of etodolac is not affected when etodolac tablets are administered after a meal. Food intake, however, reduces the peak concentration reached by approximately one-half and increases the time to peak concentration by 1.4 to 3.8 hours.

Table 1. Mean (CV%)* Pharmacokinetic Parameters of etodolac in Normal Healthy Adults and Various Special Populations
PK Parameters | Normal Healthy Adults (18-65)† (n=179) | Healthy Males (18-65) (n=176) | Healthy Females (27-65) (n=3) | Elderly (>65) (70-84) | Hemodialysis (24-65) (n=9) |  | Renal Impairment (46-73) (n=10) | Hepatic Impairment (34-60) (n=9)
 |  |  |  |  | Dialysis On | Dialysis Off
Tmax,h | 1.4 (61%)* | 1.4 (60%) | 1.7 (60%) | 1.2 (43%) | 1.7 (88%) | 0.9 (67%) | 2.1 (46%) | 1.1 (15%)
Oral Clearance, mL/ h/kg (CL/F) | 49.1 (33%) | 49.4 (33%) | 35.7 (28%) | 45.7 (27%) | NA | NA | 58.3 (19%) | 42.0 (43%)
Apparent Volume of Distribution, mL/kg (Vd/F) | 393 (29%) | 394 (29%) | 300 (8%) | 414 (38%) | NA | NA | NA | NA
Terminal Half- Life,h | 6.4 (22%) | 6.4 (22%) | 7.9 (35%) | 6.5 (24%) | 5.1 (22%) | 7.5 (34%) | NA | 5.7 (24%)
NA = not available
* % Coefficient of variation
†Age Range (years)

Distribution

The mean apparent volume of distribution (Vd/F) of etodolac is approximately 390 mL/kg. Etodolac is more than 99% bound to plasma proteins, primarily to albumin. The free fraction is less than 1% and is independent of etodolac total concentration over the dose range studied. It is not known whether etodolac is excreted in human milk; however, based on its physical-chemical properties, excretion into breast milk is expected. Data from in vitro studies, using peak serum concentrations at reported therapeutic doses in humans, show that the etodolac free fraction is not significantly altered by acetaminophen, ibuprofen, indomethacin, naproxen, piroxicam, chlorpropamide, glipizide, glyburide, phenytoin, and probenecid.

Metabolism

Etodolac is extensively metabolized in the liver. The role, if any, of a specific cytochrome P450 system in the metabolism of etodolac is unknown. Several etodolac metabolites have been identified in human plasma and urine. Other metabolites remain to be identified. The metabolites include 6-, 7-, and 8- hydroxylated-etodolac and etodolac glucuronide. After a single dose of ^14C-etodolac, hydroxylated metabolites accounted for less than 10% of total drug in serum. On chronic dosing, hydroxylated-etodolac metabolite does not accumulate in the plasma of patients with normal renal function. The extent of accumulation of hydroxylated-etodolac metabolites in patients with renal dysfunction has not been studied. The hydroxylated-etodolac metabolites undergo further glucuronidation followed by renal excretion and partial elimination in the feces.

Excretion

The mean oral clearance of etodolac following oral dosing is 49 (± 16) mL/h/kg. Approximately 1% of an etodolac dose is excreted unchanged in the urine with 72% of the dose excreted into urine as parent drug plus metabolite:

-etodolac, unchanged
-etodolac glucuronide
-hydroxylated metabolites (6-, 7-, and 8-OH)
-hydroxylated metabolite glucuronides
-unidentified metabolites

1%
13%
5%
20%
33%

Although renal elimination is a significant pathway of excretion for etodolac metabolites, no dosing adjustment in patients with mild to moderate renal dysfunction is generally necessary. The terminal half-life (t1/2) of etodolac is 6.4 hours (22% CV). In patients with severe renal dysfunction or undergoing hemodialysis, dosing adjustment is not generally necessary.

Fecal excretion accounted for 16% of the dose.

Special Populations

Geriatric

In etodolac clinical studies, no overall differences in safety or effectiveness were observed between these patients and younger patients. In pharmacokinetic studies, age was shown not to have any effect on etodolac half-life or protein binding, and there was no change in expected drug accumulation. Therefore no dosage adjustment is generally necessary in the elderly on the basis of pharmacokinetics (see PRECAUTIONS, Geriatric Use).

Etodolac is eliminated primarily by the kidney. Because elderly patients are more likely to have decreased renal function, care should be taken in dose selection, and it may be useful to monitor renal function (see WARNINGS, Renal Effects).

Pediatric

Safety and effectiveness in pediatric patients below the age of 18 years have not been established.

Race

Pharmacokinetic differences due to race have not been identified. Clinical studies included patients of many races, all of whom responded in a similar fashion.

Hepatic Insufficiency

Etodolac is predominantly metabolized by the liver. In patients with compensated hepatic cirrhosis, the disposition of total and free etodolac is not altered. Patients with acute and chronic hepatic diseases do not generally require reduced doses of etodolac compared to patients with normal hepatic function. However, etodolac clearance is dependent on liver function and could be reduced in patients with severe hepatic failure. Etodolac plasma protein binding did not change in patients with compensated hepatic cirrhosis given etodolac.

Renal Insufficiency

Etodolac pharmacokinetics have been investigated in subjects with renal insufficiency. Etodolac renal clearance was unchanged in the presence of mild-to-moderate renal failure (creatinine clearance 37 to 88 mL/min). Furthermore, there were no significant differences in the disposition of total and free etodolac in these patients. However, etodolac should be used with caution in such patients because, as with other NSAIDs, it may further decrease renal function in some patients. In patients undergoing hemodialysis, there was a 50% greater apparent clearance of total etodolac, due to a 50% greater unbound fraction. Free etodolac clearance was not altered, indicating the importance of protein binding in etodolac's disposition. Etodolac is not significantly removed from the blood in patients undergoing hemodialysis.

CLINICAL TRIALS

Analgesia

Controlled clinical trials in analgesia were single-dose, randomized, double-blind, parallel studies in three pain models, including dental extractions. The analgesic effective dose for etodolac established in these acute pain models was 200 to 400 mg. The onset of analgesia occurred approximately 30 minutes after oral administration. Etodolac 200 mg provided efficacy comparable to that obtained with aspirin (650 mg). Etodolac 400 mg provided efficacy comparable to that obtained with acetaminophen with codeine (600 mg + 60 mg). The peak analgesic effect was between 1 to 2 hours. Duration of relief averaged 4 to 5 hours for 200 mg of etodolac and 5 to 6 hours for 400 mg of etodolac as measured by when approximately half of the patients required remedication.

Osteoarthritis

The use of etodolac in managing the signs and symptoms of osteoarthritis of the hip or knee was assessed in double-blind, randomized, controlled clinical trials in 341 patients. In patients with osteoarthritis of the knee, etodolac, in doses of 600 to 1000 mg/day, was better than placebo in two studies. The clinical trials in osteoarthritis used b.i.d. dosage regimens.

Rheumatoid Arthritis

In a 3-month study with 426 patients, etodolac 300 mg b.i.d. was effective in management of rheumatoid arthritis and comparable in efficacy to piroxicam 20 mg/day. In a long-term study with 1,446 patients in which 60% of patients completed 6 months of therapy and 20% completed 3 years of therapy, etodolac in a dose of 500 mg b.i.d. provided efficacy comparable to that obtained with ibuprofen 600 mg q.i.d. In clinical trials of rheumatoid arthritis patients, etodolac has been used in combination with gold, d-penicillamine, chloroquine, corticosteroids, and methotrexate.

INDICATIONS AND USAGE

Carefully consider the potential benefits and risks of etodolac tablets, and other treatment options before deciding to use etodolac tablets. Use the lowest effective dose for the shortest duration consistent with individual patient treatment goals (see WARNINGS).

Etodolac tablets are indicated:

• For acute and long-term use in the management of signs and symptoms of the following:

1. Osteoarthritis

2. Rheumatoid arthritis

• For the management of acute pain

CONTRAINDICATIONS

Etodolac tablets are contraindicated in patients with known hypersensitivity to etodolac or other ingredients in etodolac.

Etodolac tablets should not be given to patients who have experienced asthma, urticaria, or other allergic-type reactions after taking aspirin or other NSAIDs. Severe, rarely fatal, anaphylactic-like reactions to NSAIDs have been reported in such patients (see WARNINGS, Anaphylactoid Reactions and PRECAUTIONS, Pre-existing Asthma).

- In the setting of coronary artery bypass graft (CABG) surgery [see Warnings ]

WARNINGS

CARDIOVASCULAR EFFECTS

Cardiovascular Thrombotic Events

Clinical trials of several COX-2 selective and nonselective NSAIDs of up to three years duration have shown an increased risk of serious cardiovascular (CV) thrombotic events, including myocardial infarction (MI) and stroke, which can be fatal. Based on available data, it is unclear that the risk for CV thrombotic events is similar for all NSAIDs. The relative increase in serious CV thrombotic events over baseline conferred by NSAID use appears to be similar in those with and without known CV disease or risk factors for CV disease. However, patients with known CV disease or risk factors had a higher absolute incidence of excess serious CV thrombotic events, due to their increased baseline rate. Some observational studies found that this increased risk of serious CV thrombotic events began as early as the first weeks of treatment. The increase in CV thrombotic risk has been observed most consistently at higher doses.

To minimize the potential risk for an adverse CV event in NSAID-treated patients, use the lowest effective dose for the shortest duration possible. Physicians and patients should remain alert for the development of such events, throughout the entire treatment course, even in the absence of previous CV symptoms. Patients should be informed about the symptoms of serious CV events and the steps to take if they occur.

There is no consistent evidence that concurrent use of aspirin mitigates the increased risk of serious CV thrombotic events associated with NSAID use. The concurrent use of aspirin and an NSAID, such as etodolac, increases the risk of serious gastrointestinal (GI) events [see Warnings].

Status Post Coronary Artery Bypass Graft (CABG) Surgery

Two large, controlled clinical trials of a COX-2 selective NSAID for the treatment of pain in the first 10-14 days following CABG surgery found an increased incidence of myocardial infarction and stroke. NSAIDs are contraindicated in the setting of CABG [see Contraindications].

Post-MI Patients

Observational studies conducted in the Danish National Registry have demonstrated that patients treated with NSAIDs in the post-MI period were at increased risk of reinfarction, CV-related death, and all-cause mortality beginning in the first week of treatment. In this same cohort, the incidence of death in the first year post MI was 20 per 100 person years in NSAID-treated patients compared to 12 per 100 person years in non-NSAID exposed patients. Although the absolute rate of death declined somewhat after the first year post-MI, the increased relative risk of death in NSAID users persisted over at least the next four years of follow-up.

Avoid the use of etodolac tablets in patients with a recent MI unless the benefits are expected to outweigh the risk of recurrent CV thrombotic events. If etodolac tablets are used in patients with a recent MI, monitor patients for signs of cardiac ischemia.

Hypertension

NSAIDs, including etodolac tablets, can lead to onset of new hypertension or worsening of pre-existing hypertension, either of which may contribute to the increased incidence of CV events. Patients taking thiazides or loop diuretics may have impaired response to these therapies when taking NSAIDs. NSAIDs, including etodolac tablets, should be used with caution in patients with hypertension. Blood pressure (BP) should be monitored closely during the initiation of NSAID treatment and throughout the course of therapy.

Heart Failure and Edema

The Coxib and traditional NSAID Trialists' Collaboration meta-analysis of randomized controlled trials demonstrated an approximately two-fold increase in hospitalizations for heart failure in COX-2 selective-treated patients and nonselective NSAID-treated patients compared to placebo-treated patients. In a Danish National Registry study of patients with heart failure, NSAID use increased the risk of MI, hospitalization for heart failure, and death.

Additionally, fluid retention and edema have been observed in some patients treated with NSAIDs.

Use of etodolac may blunt the CV effects of several therapeutic agents used to treat these medical conditions [e.g., diuretics, ACE inhibitors, or angiotensin receptor blockers (ARBs)] [see Drug Interactions].

Avoid the use of etodolac tablets, in patients with severe heart failure unless the benefits are expected to outweigh the risk of worsening heart failure. If etodolac tablets, are used in patients with severe heart failure, monitor patients for signs of worsening heart failure.

Gastrointestinal Effects - Risk of Ulceration, Bleeding, and Perforation

NSAIDs, including etodolac tablets, can cause serious gastrointestinal (GI) adverse events including inflammation, bleeding, ulceration, and perforation of the stomach, small intestine or large intestine, which can be fatal. These serious adverse events can occur at any time, with or without warning symptoms, in patients treated with NSAIDs. Only one in five patients, who develop a serious upper GI adverse event on NSAID therapy, is symptomatic. Upper GI ulcers, gross bleeding, or perforation caused by NSAIDs occur in approximately 1% of patients treated for 3-6 months, and in about 2-4% of patients treated for one year. These trends continue with longer duration of use, increasing the likelihood of developing a serious GI event at some time during the course of therapy. However, even short-term therapy is not without risk. Physicians should inform patients about the signs and/or symptoms of serious GI toxicity and what steps to take if they occur.

NSAIDs should be prescribed with extreme caution in those with a prior history of ulcer disease or gastrointestinal bleeding. Patients with a prior history of peptic ulcer disease, and/or gastrointestinal bleeding, and who use NSAIDs have a greater than 10-fold increased risk for developing a GI bleed compared to patients with neither of these risk factors. Other factors that increase the risk for GI bleeding in patients treated with NSAIDs include concomitant use of oral corticosteroids or anticoagulants, longer duration of NSAID therapy, smoking, use of alcohol, older age, and poor general health status. Most spontaneous reports of fatal GI events are in elderly or debilitated patients, and therefore, special care should be taken in treating this population.

To minimize the potential risk for an adverse GI event in patients treated with an NSAID, the lowest effective dose should be used for the shortest possible duration. Patients and physicians should remain alert for signs and symptoms of GI ulceration and bleeding during NSAID therapy and promptly initiate additional evaluation and treatment if a serious GI adverse event is suspected. This should include discontinuation of the NSAID until a serious GI adverse event is ruled out. For high risk patients, alternate therapies that do not involve NSAIDs should be considered.

Renal Effects

Long-term administration of NSAIDs has resulted in renal papillary necrosis and other renal injury. Renal toxicity has also been seen in patients in whom renal prostaglandins have a compensatory role in the maintenance of renal perfusion. In these patients, administration of a nonsteroidal anti-inflammatory drug may cause a dose-dependent reduction in prostaglandin formation and, secondarily, in renal blood flow, which may precipitate overt renal decompensation. Patients at greater risk of this reaction are those with impaired renal function, heart failure, liver dysfunction, those taking diuretics and ACE inhibitors, and the elderly. Discontinuation of NSAID therapy is usually followed by recovery to the pretreatment state.

Renal pelvic transitional epithelial hyperplasia, a spontaneous change occurring with variable frequency, was observed with increased frequency in treated male rats in a 2-year chronic study.

Caution is recommended in patients with pre-existing kidney disease.

Advanced Renal Disease

No information is available from controlled clinical studies regarding the use of etodolac tablets in patients with advanced renal disease. Therefore, treatment with etodolac tablets is not recommended in these patients with advanced renal disease. If etodolac tablets therapy must be initiated, close monitoring of the patient's renal function is advisable.

Anaphylactoid Reactions

As with other NSAIDs, anaphylactoid reactions may occur in patients without prior exposure to etodolac tablets. Etodolac tablets should not be given to patients with the aspirin triad. This symptom complex typically occurs in asthmatic patients who experience rhinitis with or without nasal polyps, or who exhibit severe, potentially fatal bronchospasm after taking aspirin or other NSAIDs. Fatal reactions have been reported in such patients (see CONTRAINDICATIONS and PRECAUTIONS, General, Pre-existing Asthma). Emergency help should be sought in cases where an anaphylactoid reaction occurs.

Serious Skin Reactions

NSAIDs, including etodolac, can cause serious skin adverse reactions such as exfoliative dermatitis, Stevens-Johnson Syndrome (SJS), and toxic epidermal necrolysis (TEN), which can be fatal. NSAIDs can also cause fixed drug eruption (FDE). FDE may present as a more severe variant known as generalized bullous fixed drug eruption (GBFDE), which can be life-threatening. These serious events may occur without warning. Inform patients about the signs and symptoms of serious skin reactions, and to discontinue the use of etodolac tablets at the first appearance of skin rash or any other sign of hypersensitivity. Etodolac tablets are contraindicated in patients with previous serious skin reactions to NSAIDs (see CONTRAINDICATIONS).

Drug Reaction with Eosinophilia and Systemic Symptoms (DRESS)

Drug Reaction with Eosinophilia and Systemic Symptoms (DRESS) has been reported in patients taking NSAIDs such as etodolac tablets. Some of these events have been fatal or life-threatening. DRESS typically, although not exclusively, presents with fever, rash, lymphadenopathy, and/or facial swelling. Other clinical manifestations may include hepatitis, nephritis, hematological abnormalities, myocarditis, or myositis. Sometimes symptoms of DRESS may resemble an acute viral infection. Eosinophilia is often present. Because this disorder is variable in its presentation, other organ systems not noted here may be involved. It is important to note that early manifestations of hypersensitivity, such as fever or lymphadenopathy, may be present even though rash is not evident. If such signs or symptoms are present, discontinue etodolac tablets and evaluate the patient immediately.

Fetal Toxicity

Premature Closure of Fetal Ductus Arteriosus

Avoid use of NSAIDs, including etodolac tablets, in pregnant women at about 30 weeks gestation and later. NSAIDs including etodolac tablets, increase the risk of premature closure of the fetal ductus arteriosus at approximately this gestational age.

Oligohydramnios/Neonatal Renal Impairment

Use of NSAIDs, including etodolac tablets, at about 20 weeks gestation or later in pregnancy may cause fetal renal dysfunction leading to oligohydramnios and, in some cases, neonatal renal impairment. These adverse outcomes are seen, on average, after days to weeks of treatment, although oligohydramnios has been infrequently reported as soon as 48 hours after NSAID initiation. Oligohydramnios is often, but not always, reversible with treatment discontinuation. Complications of prolonged oligohydramnios may, for example, include limb contractures and delayed lung maturation. In some postmarketing cases of impaired neonatal renal function, invasive procedures such as exchange transfusion or dialysis were required.

If NSAID treatment is necessary between about 20 weeks and 30 weeks gestation, limit etodolac tablets use to the lowest effective dose and shortest duration possible. Consider ultrasound monitoring of amniotic fluid if etodolac tablets treatment extends beyond 48 hours. Discontinue etodolac tablets if oligohydramnios occurs and follow up according to clinical practice [see PRECAUTIONS, Pregnancy].

PRECAUTIONS

General

Etodolac tablets cannot be expected to substitute for corticosteroids or to treat corticosteroid insufficiency. Abrupt discontinuation of corticosteroids may lead to disease exacerbation. Patients on prolonged corticosteroid therapy should have their therapy tapered solely if a decision is made to discontinue corticosteroids.

The pharmacological activity of etodolac tablets in reducing fever and inflammation may diminish the utility of these diagnostic signs in detecting complications of presumed noninfectious, painful conditions.

Hepatic Effects

Borderline elevations of one or more liver tests may occur in up to 15% of patients taking NSAIDs including etodolac tablets. These laboratory abnormalities may progress, may remain unchanged, or may be transient with continuing therapy. Notable elevations of ALT or AST (approximately three or more times the upper limit of normal) have been reported in approximately 1% of patients in clinical trials with NSAIDs. In addition, rare cases of severe hepatic reactions, including jaundice and fatal fulminant hepatitis, liver necrosis and hepatic failure, some of them with fatal outcomes, have been reported.

A patient with symptoms and/or signs suggesting liver dysfunction, or in whom an abnormal liver test has occurred, should be evaluated for evidence of the development of a more severe hepatic reaction while on therapy with etodolac. If clinical signs and symptoms consistent with liver disease develop, or if systemic manifestations occur (e.g., eosinophilia, rash, etc.), etodolac tablets should be discontinued.

Hematological Effects

Anemia is sometimes seen in patients receiving NSAIDs including etodolac tablets. This may be due to fluid retention, occult or gross GI blood loss, or an incompletely described effect upon erythropoiesis. Patients on long-term treatment with NSAIDs, including etodolac tablets, should have their hemoglobin or hematocrit checked if they exhibit any signs or symptoms of anemia.

NSAIDs inhibit platelet aggregation and have been shown to prolong bleeding time in some patients. Unlike aspirin, their effect on platelet function is quantitatively less, of shorter duration, and reversible. Patients receiving etodolac tablets who may be adversely affected by alterations in platelet function, such as those with coagulation disorders or patients receiving anticoagulants, should be carefully monitored.

Pre-existing Asthma

Patients with asthma may have aspirin-sensitive asthma. The use of aspirin in patients with aspirin-sensitive asthmas has been associated with severe bronchospasm which can be fatal. Since cross reactivity, including bronchospasm, between aspirin and other nonsteroidal anti-inflammatory drugs has been reported in such aspirin-sensitive patients, etodolac tablets should not be administered to patients with this form of aspirin sensitivity and should be used with caution in all patients with pre-existing asthma.

Information for Patients

Patients should be informed of the following information before initiating therapy with an NSAID and periodically during the course of ongoing therapy. Patients should also be encouraged to read the NSAID Medication Guide that accompanies each prescription dispensed.

1 Cardiovascular Thrombotic Events

Advise patients to be alert for the symptoms of cardiovascular thrombotic events, including chest pain, shortness of breath, weakness, or slurring of speech, and to report any of these symptoms to their health care provider immediately [see Warnings].

2 Etodolac tablets, like other NSAIDs, can cause GI discomfort and, rarely, serious GI side effects, such as ulcers and bleeding, which may result in hospitalization and even death. Although serious GI tract ulcerations and bleeding can occur without warning symptoms, patients should be alert for the signs and symptoms of ulcerations and bleeding, and should ask for medical advice when observing any indicative sign or symptoms including epigastric pain, dyspepsia, melena, and hematemesis. Patients should be apprised of the importance of this follow-up (see WARNINGS, Gastrointestinal Effects - Risk of Ulceration, Bleeding, and Perforation).

3 Serious Skin Reactions, including DRESS

Advise patients to stop taking tablets immediately if they develop any type of rash or fever and to contact their healthcare provider as soon as possible [see WARNINGS].

4 Heart Failure And Edema

Advise patients to be alert for the symptoms of congestive heart failure including shortness of breath, unexplained weight gain, or edema and to contact their healthcare provider if such symptoms occur [see Warnings].

5 Patients should be informed of the warning signs and symptoms of hepatotoxicity (e.g., nausea, fatigue, lethargy, pruritus, jaundice, right upper quadrant tenderness, and "flu-like" symptoms). If these occur, patients should be instructed to stop therapy and seek immediate medical therapy.

6 Patients should be informed of the signs of an anaphylactoid reaction (e.g. difficulty breathing, swelling of the face or throat). If these occur, patients should be instructed to seek immediate emergency help (see WARNINGS).

7 Fetal Toxicity

Inform pregnant women to avoid use of etodolac tablets and other NSAIDs starting at 30 weeks gestation because of the risk of the premature closing of the fetal ductus arteriosus. If treatment with etodolac tablets is needed for a pregnant woman between about 20 to 30 weeks gestation, advise her that she may need to be monitored for oligohydramnios, if treatment continues for longer than 48 hours [see WARNINGS; Fetal Toxicity, PRECAUTIONS; Pregnancy].

Laboratory Tests

Because serious GI tract ulcerations and bleeding can occur without warning symptoms, physicians should monitor for signs or symptoms of GI bleeding. Patients on long-term treatment with NSAIDs should have their CBC and a chemistry profile checked periodically for signs or symptoms of anemia. Appropriate measures should be taken in case such signs of anemia occur. If clinical signs and symptoms consistent with liver or renal disease develop, systemic manifestations occur (e.g., eosinophilia, rash, etc.) or if abnormal liver tests persist or worsen, etodolac tablets should be discontinued.

Drug Interactions

ACE-inhibitors

Reports suggest that NSAIDs may diminish the antihypertensive effect of ACE-inhibitors. This interaction should be given consideration in patients taking NSAIDs concomitantly with ACE-inhibitors (see WARNINGS).

Antacids

The concomitant administration of antacids has no apparent effect on the extent of absorption of etodolac tablets. However, antacids can decrease the peak concentration reached by 15% to 20% but have no detectable effect on the time-to-peak.

Aspirin

When etodolac is administered with aspirin, its protein binding is reduced, although the clearance of free etodolac is not altered. The clinical significance of this interaction is not known; however, as with other NSAIDs, concomitant administration of etodolac and aspirin is not generally recommended because of the potential of increased adverse effects.

Cyclosporine, Digoxin, Methotrexate

Etodolac, like other NSAIDs, through effects on renal prostaglandins, may cause changes in the elimination of these drugs leading to elevated serum levels of cyclosporine, digoxin, methotrexate, and increased toxicity. Nephrotoxicity associated with cyclosporine may also be enhanced. Patients receiving these drugs who are given etodolac, or any other NSAID, and particularly those patients with altered renal function, should be observed for the development of the specific toxicities of these drugs. NSAIDs, such as etodolac, should not be administered prior to or concomitantly with high doses of methotrexate. NSAIDs have been reported to competitively inhibit methotrexate accumulation in rabbit kidney slices. This may indicate that they could enhance the toxicity of methotrexate. In general, caution should be used when NSAIDs are administered concomitantly with methotrexate.

Diuretics

Etodolac has no apparent pharmacokinetic interaction when administered with furosemide or hydrochlorothiazide. Nevertheless, clinical studies, as well as postmarketing observations have shown that etodolac can reduce the natriuretic effect of furosemide and thiazides in some patients with possible loss of blood pressure control. This response has been attributed to inhibition of renal prostaglandin synthesis. During concomitant therapy with NSAIDs, the patient should be observed closely for signs of renal insufficiency or failure (see WARNINGS, Renal Effects), as well as to assure diuretic efficacy.

Glyburide

Etodolac has no apparent pharmacokinetic interaction when administered with glyburide.

Lithium

NSAIDs have produced an elevation of plasma lithium levels and a reduction in renal lithium clearance. The mean minimum lithium concentration increased 15% and the renal clearance was decreased by approximately 20%. These effects have been attributed to inhibition of renal prostaglandin synthesis by the NSAID. Thus, when NSAIDs and lithium are administered concurrently, subjects should be observed carefully for signs of lithium toxicity. Careful monitoring of lithium levels is advised in the event NSAID dosage adjustments are required.

Phenylbutazone

Phenylbutazone causes increase (by about 80%) in the free fraction of etodolac. Although in vivo studies have not been done to see if etodolac clearance is changed by coadministration of phenylbutazone, it is not recommended that they be coadministered.

Phenytoin

Etodolac has no apparent pharmacokinetic interaction when administered with phenytoin.

Warfarin

The effects of warfarin and NSAIDs on GI bleeding are synergistic, such that users of both drugs together have a risk of serious GI bleeding higher than that of users of either drug alone. Short-term pharmacokinetic studies have demonstrated that concomitant administration of warfarin and etodolac tablets results in reduced protein binding of warfarin, but there was no change in the clearance of free warfarin. There was no significant difference in the pharmacodynamic effect of warfarin administered alone and warfarin administered with etodolac tablets as measured by prothrombin time. Thus, concomitant therapy with warfarin and etodolac should not require dosage adjustment of either drug. However, caution should be exercised because there have been a few spontaneous reports of prolonged prothrombin times, with or without bleeding, in etodolac-treated patients receiving concomitant warfarin therapy. Close monitoring of such patients is therefore recommended.

Drug/Laboratory Test Interactions

The urine of patients who take etodolac can give a false-positive reaction for urinary bilirubin (urobilin) due to the presence of phenolic metabolites of etodolac. Diagnostic dip-stick methodology, used to detect ketone bodies in urine, has resulted in false-positive findings in some patients treated with etodolac. Generally, this phenomenon has not been associated with other clinically significant events. No dose relationship has been observed.

Etodolac treatment is associated with a small decrease in serum uric acid levels. In clinical trials, mean decreases of 1 to 2 mg/dL were observed in arthritic patients receiving etodolac (600 to 1000 mg/day) after 4 weeks of therapy. These levels then remained stable for up to 1 year of therapy.

Carcinogenesis, Mutagenesis, and Impairment of Fertility

No carcinogenic effect of etodolac was observed in mice or rats receiving oral doses of 15 mg/kg/day (45 to 89 mg/m^2, respectively) or less for periods of 2 years or 18 months, respectively. Etodolac was not mutagenic in in vitro tests performed with S. typhimurium and mouse lymphoma cells as well as in an in vivo mouse micronucleus test. However, data from the in vitro human peripheral lymphocyte test showed an increase in the number of gaps (3.0 to 5.3% unstained regions in the chromatid without dislocation) among the etodolac-treated cultures (50 to 200 mcg/mL) compared to negative controls (2.0%); no other difference was noted between the controls and drug-treated groups. Etodolac showed no impairment of fertility in male and female rats up to oral doses of 16 mg/kg (94 mg/m^2). However, reduced implantation of fertilized eggs occurred in the 8 mg/kg group.

Pregnancy

Risk Summary

Use of NSAIDs, including etodolac tablets, can cause premature closure of the fetal ductus arteriosus and fetal renal dysfunction leading to oligohydramnios and, in some cases, neonatal renal impairment. Because of these risks, limit dose and duration of etodolac tablets use between about 20 and 30 weeks of gestation, and avoid etodolac tablets use at about 30 weeks of gestation and later in pregnancy [see WARNINGS; Fetal Toxicity].

Premature Closure of Fetal Ductus Arteriosus

Use of NSAIDs, including etodolac tablets, at about 30 weeks gestation or later in pregnancy increases the risk of premature closure of the fetal ductus arteriosus.

Oligohydramnios/Neonatal Renal Impairment

Use of NSAIDs at about 20 weeks gestation or later in pregnancy has been associated with cases of fetal renal dysfunction leading to oligohydramnios, and in some cases, neonatal renal impairment.

Data from observational studies regarding other potential embryofetal risks of NSAID use in women in the first or second trimesters of pregnancy are inconclusive. In teratology studies, isolated occurrences of alterations in limb development were found and included polydactyly, oligodactyly, syndactyly, and unossified phalanges in rats and oligodactyly and synostosis of metatarsals in rabbits. These were observed at dose levels (2 to 14 mg/kg/day) close to human clinical doses. However, the frequency and the dosage group distribution of these findings in initial or repeated studies did not establish a clear drug or dose-response relationship. Animal reproduction studies are not always predictive of human response. Based on animal data, prostaglandins have been shown to have an important role in endometrial vascular permeability, blastocyst implantation, and decidualization. In animal studies, administration of prostaglandin synthesis inhibitors such as etodolac, resulted in increased pre- and post-implantation loss. Prostaglandins also have been shown to have an important role in fetal kidney development. In published animal studies, prostaglandin synthesis inhibitors have been reported to impair kidney development when administered at clinically relevant doses.

The estimated background risk of major birth defects and miscarriage for the indicated population(s) is unknown. All pregnancies have a background risk of birth defect, loss, or other adverse outcomes. In the U.S. general population, the estimated background risk of major birth defects and miscarriage in clinically recognized pregnancies is 2-4% and 15-20%, respectively.

Clinical Considerations

Fetal/Neonatal Adverse Reactions

Premature Closure of Fetal Ductus Arteriosus

Avoid use of NSAIDs in women at about 30 weeks gestation and later in pregnancy, because NSAIDs, including etodolac tablets, can cause premature closure of the fetal ductus arteriosus [see WARNINGS; Fetal Toxicity].

Oligohydramnios/Neonatal Renal Impairment

If an NSAID is necessary at about 20 weeks gestation or later in pregnancy, limit the use to the lowest effective dose and shortest duration possible. If etodolac tablets treatment extends beyond 48 hours, consider monitoring with ultrasound for oligohydramnios. If oligohydramnios occurs, discontinue etodolac tablets and follow up according to clinical practice [see WARNINGS; Fetal Toxicity].

Data

Human Data

There are no adequate and well-controlled studies in pregnant women. Etodolac tablets should be used in pregnancy only if the potential benefit justifies the potential risk to the fetus.

Premature Closure of Fetal Ductus Arteriosus

Published literature reports that the use of NSAIDs at about 30 weeks of gestation and later in pregnancy may cause premature closure of the fetal ductus arteriosus.

Oligohydramnios/Neonatal Renal Impairment

Published studies and postmarketing reports describe maternal NSAID use at about 20 weeks gestation or later in pregnancy associated with fetal renal dysfunction leading to oligohydramnios, and in some cases, neonatal renal impairment. These adverse outcomes are seen, on average, after days to weeks of treatment, although oligohydramnios has been infrequently reported as soon as 48 hours after NSAID initiation. In many cases, but not all, the decrease in amniotic fluid was transient and reversible with cessation of the drug. There have been a limited number of case reports of maternal NSAID use and neonatal renal dysfunction without oligohydramnios, some of which were irreversible. Some cases of neonatal renal dysfunction required treatment with invasive procedures, such as exchange transfusion or dialysis.

Methodological limitations of these postmarketing studies and reports include lack of a control group; limited information regarding dose, duration, and timing of drug exposure; and concomitant use of other medications. These limitations preclude establishing a reliable estimate of the risk of adverse fetal and neonatal outcomes with maternal NSAID use. Because the published safety data on neonatal outcomes involved mostly preterm infants, the generalizability of certain reported risks to the full-term infant exposed to NSAIDs through maternal use is uncertain.

Labor and Delivery

In rat studies with NSAIDs, as with other drugs known to inhibit prostaglandin synthesis, an increased incidence of dystocia, delayed parturition, and decreased pup survival occurred. The effects of etodolac tablets on labor and delivery in pregnant women are unknown.

Nursing Mothers

Trace amounts of some NSAIDs have been reported in human milk. It is not known whether etodalac is excreted in human milk. Because many drugs are excreted in human milk and because of the potential for serious adverse reactions in nursing infants from etodolac tablets, a decision should be made whether to discontinue nursing or to discontinue the drug taking into account the importance of the drug to the mother.

Pediatric Use

Safety and effectiveness in pediatric patients below the age of 18 have not been established.

Geriatric Use

As with any NSAID, caution should be exercised in treating the elderly (65 years and older) and when increasing the dose (see WARNINGS).

In etodolac tablets clinical studies, no overall differences in safety or effectiveness were observed between these patients and younger patients. In pharmacokinetic studies, age was shown not to have any effect on etodolac half-life or protein binding, and there was no change in expected drug accumulation. Therefore, no dosage adjustment is generally necessary in the elderly on the basis of pharmacokinetics (see CLINICAL PHARMACOLOGY, Special Populations).

Elderly patients may be more sensitive to the antiprostaglandin effects of NSAIDs (on the gastrointestinal tract and kidneys) than younger patients (see WARNINGS). In particular, elderly or debilitated patients who receive NSAID therapy seem to tolerate gastrointestinal ulceration or bleeding less well than other individuals, and most spontaneous reports of fatal GI events are in this population.

Etodolac is eliminated primarily by the kidney. Because elderly patients are more likely to have decreased renal function, care should be taken in dose selection, and it may be useful to monitor renal function (see WARNINGS, Renal Effects).

ADVERSE REACTIONS

In patients taking etodolac tablets or other NSAIDs, the most frequently reported adverse experiences occurring in approximately 1-10% of patients are:

Gastrointestinal experiences including: abdominal pain, constipation, diarrhea, dyspepsia, flatulence, gross bleeding/perforation, heartburn, nausea, GI ulcers (gastric/duodenal), vomiting.

Other events including: abnormal renal function, anemia, dizziness, edema, elevated liver enzymes, headaches, increased bleeding time, pruritis, rashes, tinnitus.

Adverse-reaction information for etodolac was derived from 2,629 arthritic patients treated with etodolac tablets in double-blind and open-label clinical trials of 4 to 320 weeks in duration and worldwide postmarketing surveillance studies. In clinical trials, most adverse reactions were mild and transient. The discontinuation rate in controlled clinical trials, because of adverse events, was up to 10% for patients treated with etodolac.

New patient complaints (with an incidence greater than or equal to 1%) are listed below by body system. The incidences were determined from clinical trials involving 465 patients with osteoarthritis treated with 300 to 500 mg of etodolac b.i.d. (i.e., 600 to 1000 mg/day).

Incidence Greater Than Or Equal To 1% - Probably Causally Related

Body as a whole - Chills and fever.

Digestive system - Dyspepsia (10%), abdominal pain [Drug-related patient complaints occurring in 3 to 9% of patients treated with etodolac] ., diarrhea, flatulence, nausea, abdominal distension, epigastric pain,abnormal stools, constipation, gastritis, melena, vomiting.

Nervous system - Asthenia/malaise, dizziness, depression, nervousness, fatigue.

Skin and appendages - Pruritus, rash.

Special senses - Blurred vision, tinnitus.

Urogenital system - Dysuria, urinary frequency.

Musculoskeletal - Arthralgia.

Drug-related patient complaints occurring in fewer than 3%, but more than 1%, are unmarked.

Incidence Less Than 1% - Probably Causally Related

(Adverse reactions reported only in worldwide postmarketing experience, not seen in clinical trials, are considered rarer and are italicized.)

Body as a whole - Allergic reaction, anaphylactic/anaphylactoid reactions (including shock).

Cardiovascular system - Hypertension, congestive heart failure, flushing, palpitations, syncope, vasculitis (including necrotizing and allergic).

Digestive system - Thirst, dry mouth, ulcerative stomatitis, anorexia, eructation, elevated liver enzymes, cholestatic hepatitis, hepatitis, cholestatic jaundice, duodenitis, jaundice, hepatic failure, liver necrosis, peptic ulcer with or without bleeding and/or perforation, intestinal ulceration, pancreatitis.

Hemic and lymphatic system - Ecchymosis, anemia, thrombocytopenia, bleeding time increased, agranulocytosis, hemolytic anemia, aplastic anemia, leukopenia, neutropenia, pancytopenia.

Metabolic and nutritional - Edema, serum creatinine increase, hyperglycemia in previously controlled diabetic patients.

Nervous system - Insomnia, somnolence.

Respiratory system - Asthma, pulmonary infiltration with eosinophilia.

Skin and appendages - Angioedema, sweating, urticaria, exfoliative dermatitis, vesiculobullous rash, cutaneous vasculitis with purpura, Stevens-Johnson Syndrome, toxic epidermal necrolysis, fixed drug eruption (FDE), leukocytoclastic vasculitis, hyperpigmentation, erythema multiforme.

Special senses - Photophobia, transient visual disturbances.

Urogenital system - Elevated BUN, renal failure, renal insufficiency, renal papillary necrosis.

Incidence Less Than 1% - Causal Relationship Unknown

(Medical events occurring under circumstances where causal relationship to etodolac is uncertain. These reactions are listed as alerting information for physicians.)

Body as a whole - Infection, headache.

Cardiovascular system - Arrhythmias, myocardial infarction, cerebrovascular accident.

Digestive system - Esophagitis with or without stricture or cardiospasm, colitis, GI discomfort, burning sensation, blood in stools, gastralgia, upper abdominal discomfort.

Metabolic and nutritional - Change in weight.

Nervous system - Paresthesia, confusion, irritability.

Respiratory system - Bronchitis, bronchospasm, dyspnea, pharyngitis, rhinitis, sinusitis.

Skin and appendages - Alopecia, maculopapular rash, photosensitivity, skin peeling.

Special senses - Conjunctivitis, deafness, taste perversion, loss of taste.

Urogenital system - Cystitis, hematuria, leukorrhea, renal calculus, interstitial nephritis, uterine bleeding irregularities, renal impairment.

Musculoskeletal - Muscle pain.

Additional Adverse Reactions Reported with NSAIDs

Body as a whole - Sepsis, death

Cardiovascular system - Tachycardia

Digestive system - Gastric ulcers, gastritis, gastrointestinal bleeding, glossitis, hematemesis

Hemic and lymphatic system - Lymphadenopathy

Nervous system - Anxiety, dream abnormalities, convulsions, coma, hallucinations, meningitis, tremors, vertigo

Respiratory system - Respiratory depression, pneumonia

Urogenital system - Oliguria/polyuria, proteinuria

OVERDOSAGE

Symptoms following acute NSAID overdose are usually limited to lethargy, drowsiness, nausea, vomiting, and epigastric pain, which are generally reversible with supportive care. Gastrointestinal bleeding can occur and coma has occurred following massive ibuprofen or mefenamic-acid overdose. Hypertension, acute renal failure, and respiratory depression may occur but are rare. Anaphylactoid reactions have been reported with therapeutic ingestion of NSAIDs, and may occur following overdose.

Patients should be managed by symptomatic and supportive care following an NSAID overdose. There are no specific antidotes. Emesis and/or activated charcoal (60 to 100 g in adults, 1 to 2 g/kg in children) and/or osmotic cathartic may be indicated in patients seen within 4 hours of ingestion with symptoms or following a large overdose (5 to 10 times the usual dose). Forced diuresis, alkalinization of the urine, hemodialysis, or hemoperfusion would probably not be useful due to etodolac's high protein binding.

DOSAGE AND ADMINISTRATION

Carefully consider the potential benefits and risks of etodolac tablets and other treatment options before deciding to use etodolac tablets. Use the lowest effective dose for the shortest duration consistent with individual patient treatment goals (see WARNINGS).

After observing the response to initial therapy with etodolac tablets, the dose and frequency should be adjusted to suit an individual patient's needs.

Dosage adjustment of etodolac tablets is generally not required in patients with mild to moderate renal impairment. Etodolac should be used with caution in such patients, because, as with other NSAIDs, it may further decrease renal function in some patients with impaired renal function (see WARNINGS, Renal Effects).

Analgesia

The recommended total daily dose of etodolac for acute pain is up to 1000 mg, given as 200-400 mg every 6 to 8 hours. Doses of etodolac greater than 1000 mg/day have not been adequately evaluated in well-controlled trials.

Osteoarthritis and Rheumatoid Arthritis

The recommended starting dose of etodolac for the management of the signs and symptoms of osteoarthritis or rheumatoid arthritis is: 300 mg b.i.d., t.i.d., or 400 mg b.i.d., or 500 mg b.i.d. A lower dose of 600 mg/day may suffice for long-term administration. Physicians should be aware that doses above 1000 mg/day have not been adequately evaluated in well-controlled clinical trials.

In chronic conditions, a therapeutic response to therapy with etodolac is sometimes seen within one week of therapy, but most often is observed by two weeks. After a satisfactory response has been achieved, the patient's dose should be reviewed and adjusted as required.

HOW SUPPLIED

Etodolac tablets, USP are available as:

Etodolac tablets, USP 400 mg are brown colored oval shaped film coated tablets debossed with '49' on one side and 'I' on other side

NDC 83980-029-13 Bottle of 30's

NDC 83980-029-01 Bottle of 100's

NDC 83980-029-10 Bottle of 1,000's

Etodolac tablets, USP 500 mg are yellow colored oval shaped film coated tablets debossed with '48' on one side and 'I' on other side

NDC 83980-030-13 Bottle of 30's

NDC 83980-030-01 Bottle of 100's

NDC 83980-030-05 Bottle of 500's

Store at 20ºC to 25ºC (68ºF to 77ºF) [See USP Controlled Room Temperature].Store tablets inoriginal container until ready to use. Dispense in light-resistant container.

You may report side eff ects to Ipca at 1-888-472-2651 or FDA at 1-800-FDA-1088.

Additional medication guides can be obtained by calling Ipca at 1-888-472-2651.

Distributed by:

Unichem Pharmaceuticals (USA), Inc.

East Brunswick,

NJ 08816, USA

January 2025

IEPON1

Medication Guide for Nonsteroidal Anti-Inflammatory Drugs (NSAIDs)

What is the most important information I should know about medicines called Nonsteroidal Anti-Inflammatory Drugs (NSAIDs)?
NSAIDs can cause serious side effects, including:

- Increased risk of a heart attack or stroke that can lead to death. This risk may happen early in treatment and may increase:

o with increasing doses of NSAIDs
o with longer use of NSAIDs
Do not take NSAIDs right before or after a heart surgery called a "coronary artery bypass graft (CABG)."
Avoid taking NSAIDs after a recent heart attack, unless your healthcare provider tells you to. You may have an increased risk of another heart attack if you take NSAIDs after a recent heart attack.

- Increased risk of bleeding, ulcers , and tears (perforation) of the esophagus (tube leading from the mouth to the stomach), stomach and intestines :

o anytime during use
o without warning symptoms
o that may cause death
The risk of getting an ulcer or bleeding increases with:

o past history of stomach ulcers, or stomach or intestinal bleeding with use of NSAIDs

o taking medicines called "corticosteroids", "anticoagulants", "SSRIs", or "SNRIs"

o increasing doses of NSAIDs

○ older age

o longer use of NSAIDs

○ poor health

o smoking

○ advanced liver disease

o drinking alcohol

○ bleeding problems

NSAIDs should only be used:
o exactly as prescribed
o at the lowest dose possible for your treatment
o for the shortest time needed

What are NSAIDs?
NSAIDs are used to treat pain and redness, swelling, and heat (inflammation) from medical conditions such as different types of arthritis, menstrual cramps, and other types of short-term pain.

Who should not take NSAIDs?
Do not take NSAIDs:

- if you had an asthma attack, hives, or other allergic reaction with aspirin or any other NSAIDs.
- right before or after heart bypass surgery.

Before taking NSAIDs, tell your healthcare provider about all of your medical conditions, including if you:

- have liver or kidney problems
- have high blood pressure
- have asthma
- are pregnant or plan to become pregnant. Taking NSAIDs at about 20 weeks of pregnancy or later may harm your unborn baby. If you need to take NSAIDs for more than 2 days when you are between 20 and 30 weeks of pregnancy, your healthcare provider may need to monitor the amount of fluid in your womb around your baby. You should not take NSAIDs after 30 weeks of pregnancy.
- are breastfeeding or plan to breast feed.

Tell your healthcare provider about all of the medicines you take, including prescription or over-the-counter medicines, vitamins or herbal supplements. NSAIDs and some other medicines can interact with each other and cause serious side effects. Do not start taking any new medicine without talking to your healthcare provider first.

What are the possible side effects of NSAIDs?
NSAIDs can cause serious side effects, including:
See "What is the most important information I should know about medicines called Nonsteroidal Anti-inflammatory Drugs (NSAIDs)?

- new or worse high blood pressure

- heart failure
- liver problems including liver failure
- kidney problems including kidney failure
- low red blood cells (anemia)
- life-threatening skin reactions
- life-threatening allergic reactions
- Other side effects of NSAIDs include: stomach pain, constipation, diarrhea, gas, heartburn, nausea, vomiting, and dizziness.

Get emergency help right away if you get any of the following symptoms :

- shortness of breath or trouble breathing

- chest pain

- slurred speech

- weakness in one part or side of your body

- swelling of the face or throat

Stop taking your NSAID and call your healthcare provider right away if you get any of the following symptoms:

- nausea

- vomit blood

- more tired or weaker than usual

- there is blood in your bowel movement or it is black and sticky like tar

- diarrhea

- unusual weight gain

- itching

- skin rash or blisters with fever

- your skin or eyes look yellow

- swelling of the arms, legs, hands and feet

- indigestion or stomach pain

- flu-like symptoms

If you take too much of your NSAID, call your healthcare provider or get medical help right away.
These are not all the possible side effects of NSAIDs. For more information, ask your healthcare provider or pharmacist about NSAIDs.
Call your doctor for medical advice about side effects. You may report side effects to FDA at 1-800-FDA-1088.

Other information about NSAIDs

- Aspirin is an NSAID but it does not increase the chance of a heart attack. Aspirin can cause bleeding in the brain, stomach, and intestines. Aspirin can also cause ulcers in the stomach and intestines.
- Some NSAIDs are sold in lower doses without a prescription (over–the–counter). Talk to your healthcare provider before using over–the–counter NSAIDs for more than 10 days.

General information about the safe and effective use of NSAIDs
Medicines are sometimes prescribed for purposes other than those listed in a Medication Guide. Do not use NSAIDs for a condition for which it was not prescribed. Do not give NSAIDs to other people, even if they have the same symptoms that you have. It may harm them.
If you would like more information about NSAIDs, talk with your healthcare provider. You can ask your pharmacist or healthcare provider for information about NSAIDs that is written for health professionals.

This Medication Guide has been approved by the U.S. Food and Drug Administration.

Additional medication guides can be obtained by calling Ipca at 1-888-472-2651.

Distributed by:

Unichem Pharmaceuticals (USA), Inc.

East Brunswick,

NJ 08816, USA

January 2025

IEPONI

PACKAGE LABEL.PRINCIPAL DISPLAY PANEL

NDC 83980-029-01

Etodolac Tablets, USP

400 mg

PHARMACIST: Dispense the accompanying Medication Guide to each patient.

100 Tablets

Rx only

NDC 83980-030-01

Etodolac Tablets, USP

500 mg

PHARMACIST: Dispense the accompanying Medication Guide to each patient.

100 Tablets

Rx only